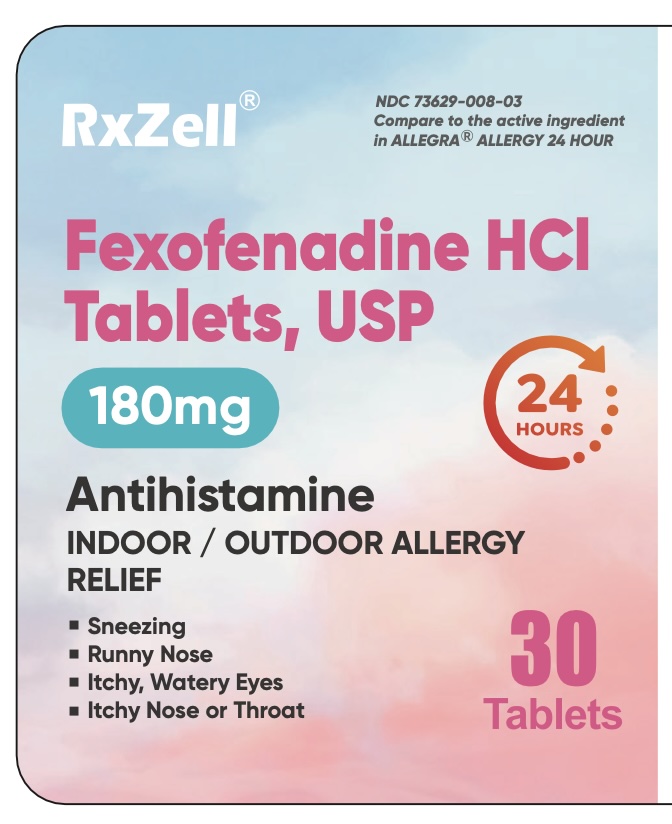 DRUG LABEL: Fexofenadine Hydrochloride
NDC: 73629-008 | Form: TABLET, FILM COATED
Manufacturer: AMZ789 LLC
Category: otc | Type: HUMAN OTC DRUG LABEL
Date: 20260107

ACTIVE INGREDIENTS: FEXOFENADINE HYDROCHLORIDE 180 mg/1 1
INACTIVE INGREDIENTS: FERROSOFERRIC OXIDE; FERRIC OXIDE RED; HYPROMELLOSE 2910 (15 MPA.S); TITANIUM DIOXIDE; FERRIC OXIDE YELLOW; CROSCARMELLOSE SODIUM; MICROCRYSTALLINE CELLULOSE; LACTOSE MONOHYDRATE; MAGNESIUM STEARATE; POLYETHYLENE GLYCOL 6000; STARCH, CORN; SILICON DIOXIDE

Fexofenadine HCl Tablets USP 180 mg

ACTIVE INGREDIENT(S)

Fexofenadine HCl USP 180 mg

PURPOSE

Antihistamine

USE(S)

temporarily relieves these symptoms due to hay fever or other upper respiratory allergies:

- runny nose
- itchy, water eyes
- sneezing
- itching of the nose or throat

INDICATIONS AND USAGE

temporarily relieves these symptoms due to hay fever or other upper respiratory allergies:

- runny nose
- itchy, water eyes
- sneezing
- itching of the nose or throat

WARNINGS

Do not use.

if you have ever had an allergic reaction to this product or any of its ingredients.

Ask a doctor before use if you have
kidney disease. Your doctor should determine if you need a different dose.

When using this product

- do not take more than directed
- do not take at the same time as aluminum or magnesium antacids
- do not take with fruit juices (see Directions)

Stop use and ask a doctor if
an allergic reaction to this product occurs. Seek medical help right away.

If pregnant or breast-feeding
ask a health professional before use.

Keep out of reach of children

In case of overdose, get medical help or contact a Poison Control Center right away.

Directions

adults and children 12 years of age and over | take one 180 mg tablet with water once a day; do not take more than 1 tablet in 24 hours (for 180 mg)
children under 12 years of age | do not use
adults 65 years of age and older | ask a doctor
consumers with kidney disease | ask a doctor

OTHER INFORMATION

- Safety-sealed: do not use if foil printed with granules logo under bottle cap is opened or torn.
- Do not use if carton is opened or if individual blister units are torn or opened.
- store between 20º and 25ºC (68º and 77ºF)
- protect from excessive moisture

Inactive Ingredients

colloidal silicon dioxide, croscarmellose sodium, hypromellose, iron oxide black, iron oxide red, iron oxide yellow, lactose monohydrate, macrogol, magnesium stearate, microcrystalline cellulose, pregelatinized starch, titanium dioxide.